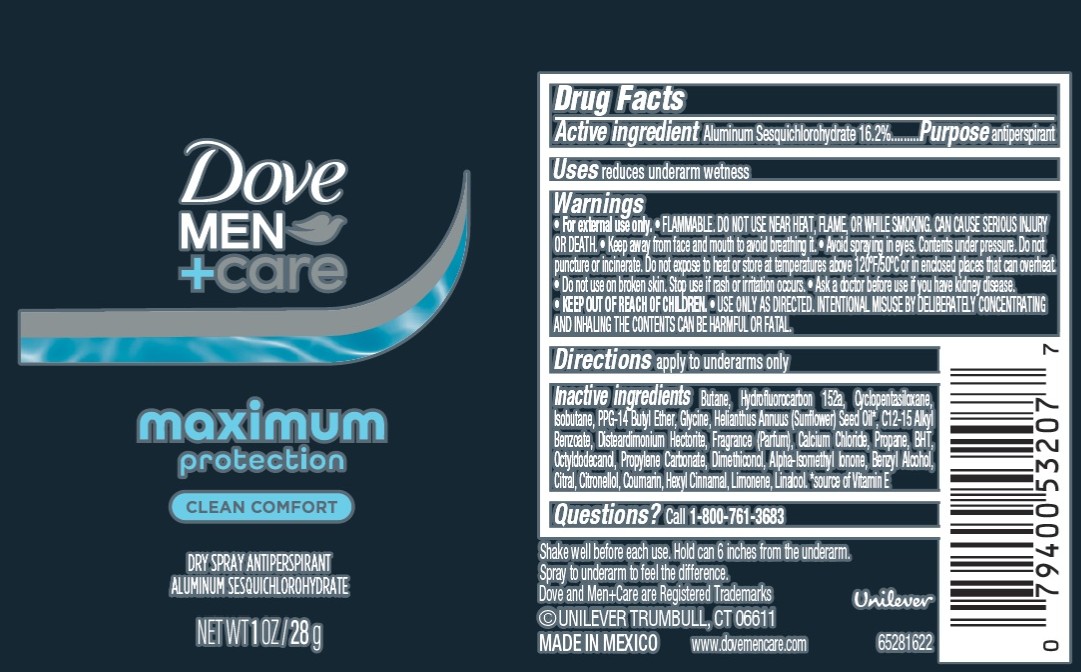 DRUG LABEL: Dove Men Care
NDC: 64942-2418 | Form: AEROSOL, SPRAY
Manufacturer: Conopco d/b/a Unilever
Category: otc | Type: HUMAN OTC DRUG LABEL
Date: 20251218

ACTIVE INGREDIENTS: ALUMINUM SESQUICHLOROHYDRATE 16.2 g/100 g
INACTIVE INGREDIENTS: ISOBUTANE; CITRONELLOL; BUTANE; PPG-14 BUTYL ETHER; GLYCINE; HELIANTHUS ANNUUS (SUNFLOWER) SEED OIL; LIMONENE, (+)-; HYDROFLUOROCARBON 152A; C12-15 ALKYL BENZOATE; DISTEARDIMONIUM HECTORITE; CALCIUM CHLORIDE; PROPANE; BHT; DIMETHICONOL (40 CST); ALPHA-ISOMETHYL IONONE; BENZYL ALCOHOL; CITRAL; COUMARIN; HEXYL CINNAMAL; LINALOOL; CYCLOPENTASILOXANE; OCTYLDODECANOL; PROPYLENE CARBONATE

Dove Men + Care Maximum Protection Clean Comfort Dry Spray Antiperspirant

DESCRIPTION

Dove Men + Care Maximum Protection Clean Comfort Dry Spray Antiperspirant

ACTIVE INGREDIENT

Aluminum Sesquichlorohydrate 16.2%

PURPOSE

Antiperspirant

INDICATIONS AND USAGE

reduces underarm wetness

WARNINGS

• For external use only.
• FLAMMABLE. DO NOT USE NEAR HEAT, FLAME, OR WHILE SMOKING. CAN CAUSE SERIOUS INJURY OR DEATH.
• Keep away from face and mouth to avoid breathing it.
• Avoid spraying in eyes. Contents under pressure. Do not puncture or incinerate. Do not expose to heat or store at temperatures above 120°F/50°C or in enclosed places that can overheat.

• KEEP OUT OF REACH OF CHILDREN.

DOSAGE AND ADMINISTRATION

apply to underarms only

INACTIVE INGREDIENT

Butane, Hydrofluorocarbon 152a, Cyclopentasiloxane,
Isobutane, PPG-14 Butyl Ether, Glycine, Helianthus Annuus (Sunflower) Seed Oil, C12-15 Alkyl
Benzoate, Disteardimonium Hectorite, Fragrance (Parfum), Calcium Chloride, Propane, BHT,
Octyldodecanol, Propylene Carbonate, Dimethiconol, Alpha-Isomethyl Ionone, Benzyl Alcohol,
Citral, Citronellol, Coumarin, Hexyl Cinnamal, Limonene, Linalool.

QUESTIONS

Call 1-800-761-3683